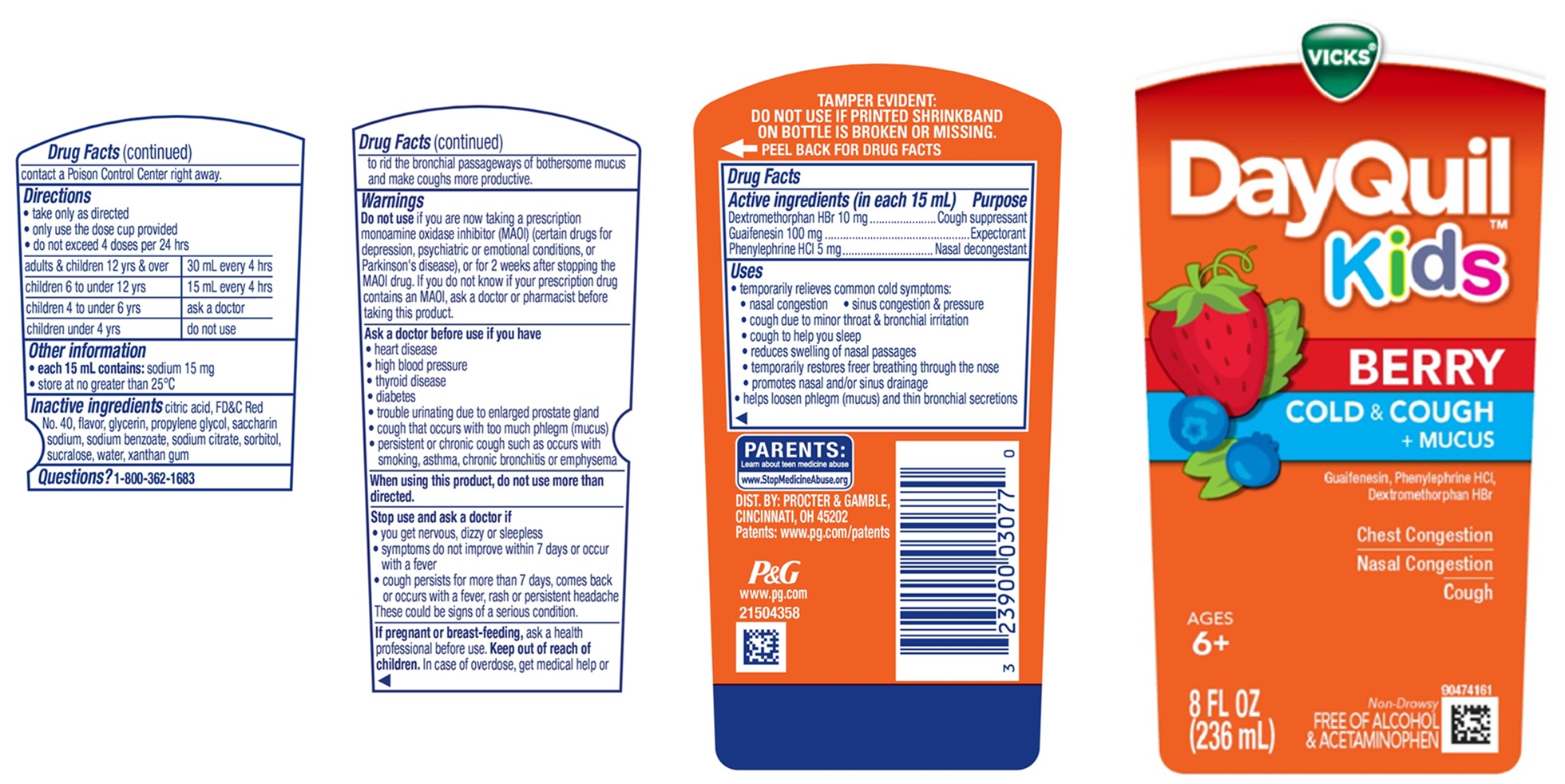 DRUG LABEL: Vicks DayQuil Kids BERRY
NDC: 69423-778 | Form: LIQUID
Manufacturer: The Procter & Gamble Manufacturing Company
Category: otc | Type: HUMAN OTC DRUG LABEL
Date: 20260211

ACTIVE INGREDIENTS: DEXTROMETHORPHAN HYDROBROMIDE 10 mg/15 mL; PHENYLEPHRINE HYDROCHLORIDE 5 mg/15 mL; GUAIFENESIN 100 mg/15 mL
INACTIVE INGREDIENTS: XANTHAN GUM; ANHYDROUS CITRIC ACID; PROPYLENE GLYCOL; WATER; SACCHARIN SODIUM; SODIUM CITRATE; SORBITOL; FD&C RED NO. 40; GLYCERIN; SODIUM BENZOATE; SUCRALOSE

Vicks® DayQuil™ Kids BERRY COLD & COUGH + MUCUS

Drug Facts

Active ingredients (in each 15 mL)

Dextromethorphan HBr 10 mg

Guaifenesin 100 mg

Phenylephrine HCl 5 mg

Active ingredients (in each 15 mL) Purpose

Cough suppressant

Expectorant

Nasal decongestant

Uses

• temporarily relieves common cold symptoms:

- nasal congestion • sinus congestion & pressure
- cough due to minor throat & bronchial irritation
- cough to help you sleep
- reduces swelling of nasal passages
- temporarily restores freer breathing through the nose
- promotes nasal and/or sinus drainage

• helps loosen phlegm (mucus) and thin bronchial secretions to rid the bronchial passageways of bothersome mucus
and make coughs more productive.

Warnings

Do not use if you are now taking a prescription monoamine oxidase inhibitor (MAOI) (certain drugs for depression, psychiatric or emotional conditions, or Parkinson's disease), or for 2 weeks after stopping the MAOI drug. If you do not know if your prescription drug contains an MAOI, ask a doctor or pharmacist before taking this product.

Ask a doctor before use if you have

- heart disease
- high blood pressure
- thyroid disease
- diabetes
- trouble urinating due to enlarged prostate gland
- cough that occurs with too much phlegm (mucus)
- persistent or chronic cough such as occurs with smoking, asthma, chronic bronchitis or emphysema

Stop use and ask a doctor if

- you get nervous, dizzy or sleepless
- symptoms do not improve within 7 days or occur with a fever
- cough persists for more than 7 days, comes back or occurs with a fever, rash or persistent headache

These could be signs of a serious condition.

If pregnant or breast-feeding

ask a health professional before use.

Keep out of reach of children.

In case of overdose, get medical help or contact a Poison Control Center right away.

Directions

• take only as directed

• only use the dose cup provided

• do not exceed 4 doses per 24 hrs

adults & children 12 yrs & over | 30 mL every 4 hrs
children 6 to under 12 yrs | 15 mL every 4 hrs
children 4 to under 6 yrs | ask a doctor
children under 4 yrs | do not use

Other information

- each 15 mL contains:sodium 15 mg
- store at no greater than 25°C

Inactive ingredients

citric acid, FD&C Red No. 40, flavor, glycerin, propylene glycol, saccharin sodium, sodium benzoate, sodium citrate, sorbitol, sucralose, water, xanthan gum

Questions?

1-800-362-1683

TAMPER EVIDENT: DO NOT USE IF PRINTED SHRINKBAND ON BOTTLE IS BROKEN OR MISSING.

DIST. BY: PROCTER & GAMBLE, CINCINNATI, OH 45202

PRINCIPAL DISPLAY PANEL - 236 mL Bottle Label

Vicks® DayQuil™ Kids BERRY

COLD & COUGH + MUCUS

Guaifenesin, Phenylephrine HCl, Dextromethorphan HBr

Chest Congestion

Nasal Congestion

Cough

AGES 6+

Non-Drowsy

FREE OF ALCOHOL & ACETAMINOPHEN

8 FL OZ (236 mL)